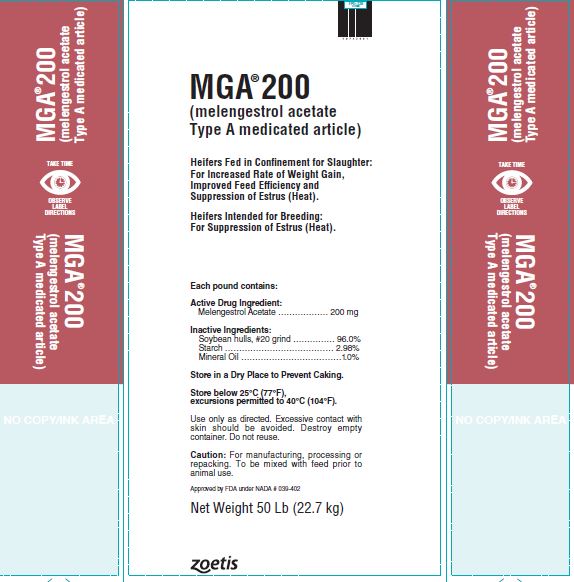 DRUG LABEL: MGA
NDC: 54771-1952 | Form: GRANULE
Manufacturer: Zoetis Inc.
Category: animal | Type: OTC ANIMAL DRUG LABEL
Date: 20210512

ACTIVE INGREDIENTS: MELENGESTROL ACETATE 200 mg/0.45 kg

MGA® 200

MGA® 200

(melengestrol acetate Type A medicated article)

Heifers Fed in Connement for Slaughter:

For Increased Rate of Weight Gain, Improved Feed Efficiency and Suppression of Estrus (Heat).

Heifers Intended for Breeding:

For Suppression of Estrus (Heat).

Each pound contains:

Active Drug Ingredient:

Melengestrol Acetate ……………… 200 mg

Inactive Ingredients:

Soybean hulls, #20 grind …………… 96.0%

Starch ………………………………… 2.98%

Mineral Oil ………………………………1.0%

Store in a Dry Place to Prevent Caking.

Store below 25°C (77°F), excursions permitted to 40°C (104°F).
Use only as directed. Excessive contact with skin should be avoided. Destroy empty container. Do not reuse.
Caution: For manufacturing, processing or repacking. To be mixed with feed prior to animal use.
Approved by FDA under NADA # 039-402
Net Weight 50 Lb (22.7 kg)

DIRECTIONS FOR USE:

Heifers Fed in Confinement for Slaughter: MGA 200 (melengestrol acetate Type A medicated article) should be thoroughly mixed in the supplement to provide 0.25 to 0.50 mg of melengestrol acetate per head per day. Average daily intakes approximating the middle of this range provide the most optimal and economical improvements in rate of gain and feed utilization. Constant daily intakes of 0.35 to 0.50 mg per head per day give a high degree of estrus suppression. Levels of 0.25 to 0.35 mg provide a lower but still effective degree of estrus suppression.

Heifers Intended for Breeding: MGA 200 should be thoroughly mixed in the supplement to provide 0.5 mg of melengestrol acetate per head per day.

NOT FOR HUMAN USE.

CAUTION: Not effective in steers and spayed heifers.

Heifers Fed in Confinement for Slaughter: Withdrawal periods of three to five days or more should be avoided to prevent the possibility that the heifers may come into estrus (heat) at loading time.

Heifers Intended for Breeding:

Do not exceed 24 days of feeding of melengestrol acetate to heifers intended for breeding. A reduced conception rate can be expected if heifers are bred at estruses observed within 1 to 12 days after withdrawal of melengestrol acetate, whereas heifers bred at subsequent observed estruses are expected to have normal conception rates.

Mixing Directions

Thoroughly mix 1.25 to 10 pounds of MGA 200 per ton of non-medicated feed to prepare a Type C medicated feed containing 0.25 to 2.0 grams of melengestrol acetate per ton. The following Table may be used as a guide in determining the amount of MGA 200 to be added to prepare a ton of Type C medicated feed.

Amount of Type C Feed Fed (lb/head/day) | Melengestrol Acetate (mg/head/day) | Pounds MGA 200 per Ton of Type C Feed
0.5 | 0.25 | 5.00
0.5 | 0.30 | 6.00
0.5 | 0.35 | 7.00
0.5 | 0.40 | 8.00
0.5 | 0.45 | 9.00
0.5 | 0.50 | 10.00
1.0 | 0.25 | 2.50
1.0 | 0.30 | 3.00
1.0 | 0.35 | 3.50
1.0 | 0.40 | 4.00
1.0 | 0.45 | 4.50
1.0 | 0.50 | 5.00
1.5 | 0.25 | 1.67
1.5 | 0.30 | 2.00
1.5 | 0.35 | 2.33
1.5 | 0.40 | 2.67
1.5 | 0.45 | 3.00
1.5 | 0.50 | 3.33
2.0 | 0.25 | 1.25
2.0 | 0.30 | 1.50
2.0 | 0.35 | 1.75
2.0 | 0.40 | 2.00
2.0 | 0.45 | 2.25
2.0 | 0.50 | 2.50

Type B medicated feeds containing 4 to 10 grams melengestrol acetate per ton may be manufactured by thoroughly mixing 20 to 50 lbs of MGA 200 with 1980 to 1950 lbs of non-medicated feed. Labeling for such Type B feeds shall contain directions for manufacturing Type C medicated feeds containing 0.25 to 2.0 grams melengestrol acetate per ton (0.125–1.0 mg/lb). The Type C medicated feed, containing melengestrol acetate, must be top dressed on grain or roughage or mixed with a complete ration at the rate of 0.5 to 2.0 pounds per head per day.

Good manufacturing practice regulations must be adhered to in manufacturing feeds containing MGA 200.

Restricted Drug (California)—Use Only as Directed
zoetis
Distributed by:
Zoetis Inc.
Kalamazoo, MI 49007
50743801